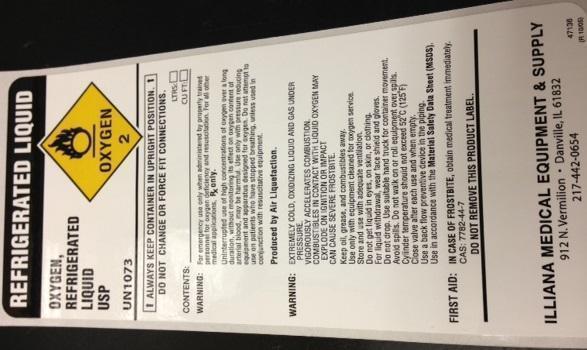 DRUG LABEL: Oxygen
NDC: 59470-001 | Form: GAS
Manufacturer: Steve Gulick, Inc.
Category: prescription | Type: HUMAN PRESCRIPTION DRUG LABEL
Date: 20131029

ACTIVE INGREDIENTS: OXYGEN 990 mL/1 L

Oxygen

PACKAGE LABEL

UN1073 OXYGEN, REFRIGERATED LIQUID USP

ALWAYS KEEP CONTINER IN UPRIGHT POSITION. DO NOT CHANGE OR FORCE-FIT CONNECTIONS

CONTENTS

WARNING: For emergency use only when administered by properly trained personnel for oxygen deficiency and resuscitation. For all other medical applications, Rx ONLY.

Uninterrupted use of high concentrations of oxygen over a long duration, without monitoring its effects on oxygen content of arterial blood, may be harmful. Use only with pressure reducing equipment and apparatus designed for oxygen. Do not attempt to use on patients who have stopped breathing unless used in conjunction with resuscitative equipment.

Produced by Air Liquefaction

WARNING! EXTREMELY COLD, OXIDIZING LIQUID AND GAS UNDER PRESSURE. VIGOROUSLY ACCELERATES COMBUSTION. COMBUSTIBLES IN CONTACT WITH

LIQUID OXYGEN MAY EXPLODE ON IGNITION OR IMPACT. CAN CAUSE SEVERE FROSTBITE.

Keep oil, grease, and combustibles away. Use with equipment cleaned for oxygen service. Store and use with adequate ventilation do not get liquid in eyes, on skin, or clothing. For liquid withdrawal, wear face shield and gloves. Do not drop .Use suitable hand truck for container movement.

Avoid spills. Do not walk on or roll equipment over spills

Cylinder temperature should not exceed 125°F (52°C)

Close valve after each use and when empty.

Use backflow preventative device in the piping.

Use in accordance with the Material Safety Data Sheet (MSDS)

FIRST AID: IN CASE OF FROSTBITE obtain medical treatment immediately. CAS 7782-44-7

DO NOT REMOVE THIS LABEL

ILLIANA MEDICAL EQUIPMENT and SUPPLY

912 Vermillion * Danville, IL 61832

217-442-0654

47136

(R1005)